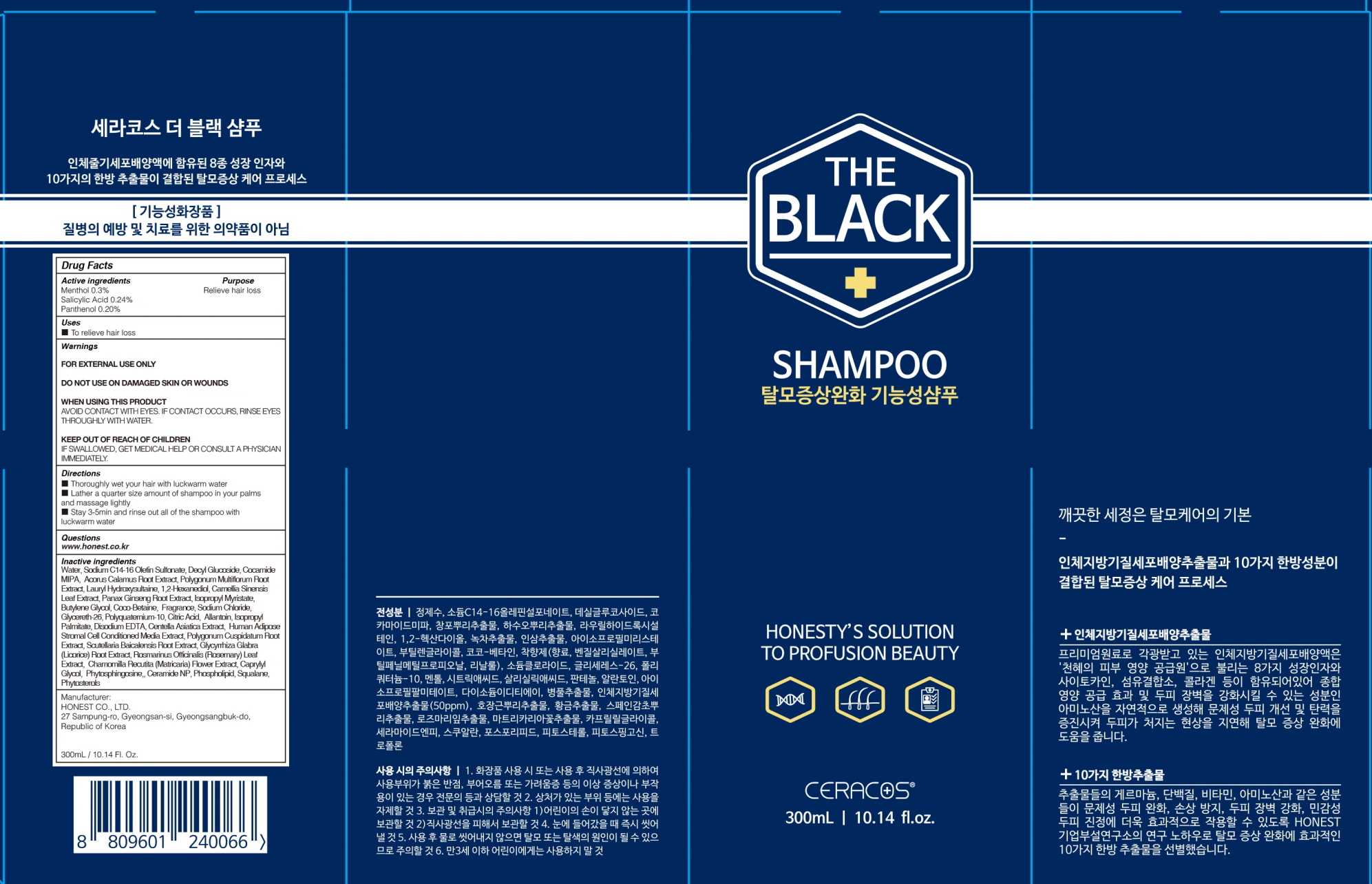 DRUG LABEL: CERACOS THE BLACK
NDC: 76904-010 | Form: SHAMPOO
Manufacturer: Honest Co., Ltd.
Category: otc | Type: HUMAN OTC DRUG LABEL
Date: 20200501

ACTIVE INGREDIENTS: Menthol 0.90 g/300 mL; Salicylic Acid 0.72 g/300 mL; Panthenol 0.60 g/300 mL
INACTIVE INGREDIENTS: Water; Sodium C14-16 Olefin Sulfonate; Decyl Glucoside; 1,2-Hexanediol; Glycereth-26

ACTIVE INGREDIENT

Active ingredients: Menthol 0.3%, Salicylic Acid 0.24%, Panthenol 0.20%

INACTIVE INGREDIENT

Inactive ingredients:
Water, Sodium C14-16 Olefin Sulfonate, Decyl Glucoside, Cocamide MIPA, Acorus Calamus Root Extract, Polygonum Multiflorum Root Extract, Lauryl Hydroxysultaine, 1,2-Hexanediol, Camellia Sinensis Leaf Extract, Panax Ginseng Root Extract, Isopropyl Myristate, Butylene Glycol, Coco-Betaine, Fragrance, Sodium Chloride, Glycereth-26, Polyquaternium-10, Citric Acid, Allantoin, Isopropyl Palmitate, Disodium EDTA, Centella Asiatica Extract, Human Adipose Stromal Cell Conditioned Media Extract, Polygonum Cuspidatum Root Extract, Scutellaria Baicalensis Root Extract, Glycyrrhiza Glabra (Licorice) Root Extract, Rosmarinus Officinalis (Rosemary) Leaf Extract, Chamomilla Recutita (Matricaria) Flower Extract, Caprylyl Glycol, Phytosphingosine,, Ceramide NP, Phospholipid, Squalane, Phytosterols, Tropolone

PURPOSE

Purpose: Relieve hair loss

WARNINGS

FOR EXTERNAL USE ONLY

DO NOT USE ON DAMAGED SKIN OR WOUNDS

WHEN USING THIS PRODUCT
AVOID CONTACT WITH EYES. IF CONTACT OCCURS, RINSE EYES THROUGHLY WITH WATER.

KEEP OUT OF REACH OF CHILDREN

IF SWALLOWED, GET MEDICAL HELP OR CONSULT A PHYSICIAN IMMEDIATELY.

Uses

■ To relieve hair loss

Directions

■ Thoroughly wet your hair with luckwarm water
■ Lather a quarter size amount of shampoo in your palms and massage lightly
■ Stay 3-5min and rinse out all of the shampoo with luckwarm water

QUESTIONS

■ www.honest.co.kr